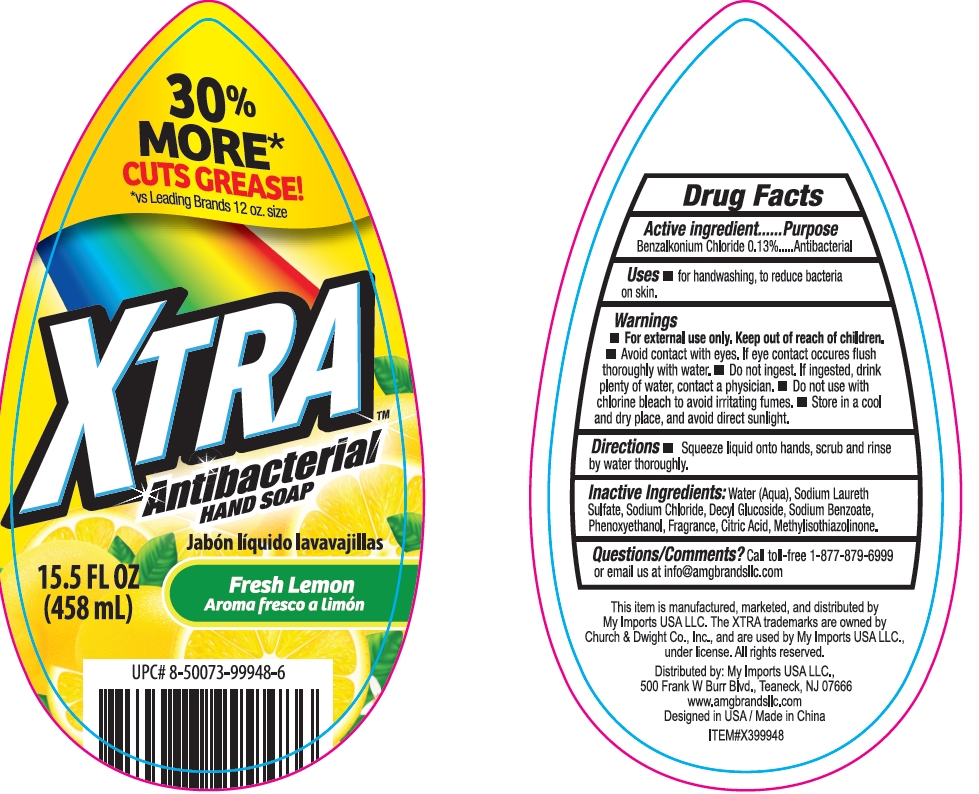 DRUG LABEL: XTRA Squeeze Antibacterial Hand Fresh Lemon
NDC: 51628-4502 | Form: GEL
Manufacturer: MY IMPORTS USA LLC.
Category: otc | Type: HUMAN OTC DRUG LABEL
Date: 20250710

ACTIVE INGREDIENTS: BENZALKONIUM CHLORIDE 0.13 g/100 mL
INACTIVE INGREDIENTS: PHENOXYETHANOL; METHYLISOTHIAZOLINONE; DECYL GLUCOSIDE; SODIUM BENZOATE; AQUA; SODIUM LAURETH SULFATE; CITRIC ACID; SODIUM CHLORIDE

XTRA Squeeze Antibacterial Hand Soap Fresh Lemon

Active Ingredient

Benzalkonium Chloride 0.13%

Purpose

Antibacterial

Uses

For handwashing, to reduce bacteria on skin

Warnings

For external use only.

Keep out of reach of children

Keep out of reach od children

DO NOT USE

Avoid contact with eyes. If eye contact occures flush thoroughly with water.

Do not use with chlorine bleach to avoid irritating fumes.

ASK DOCTOR

Do not ingest. If ingested, drink plenty of water, contact a physician.

STORAGE AND HANDLING

Store in a cool and dry place, and avoid direct sunlight.

Directions

Squeeze liquid onto hands, scrub and rinse by water thoroughly.

Inactive ingredients

Water (Aqua)

Sodium Laureth Sulfate

Sodium Chloride

Decyl Glucoside

Sodium Benzoate

Phenoxyethanol

Fragrance

Citric Acid

Methylisothiazlinone